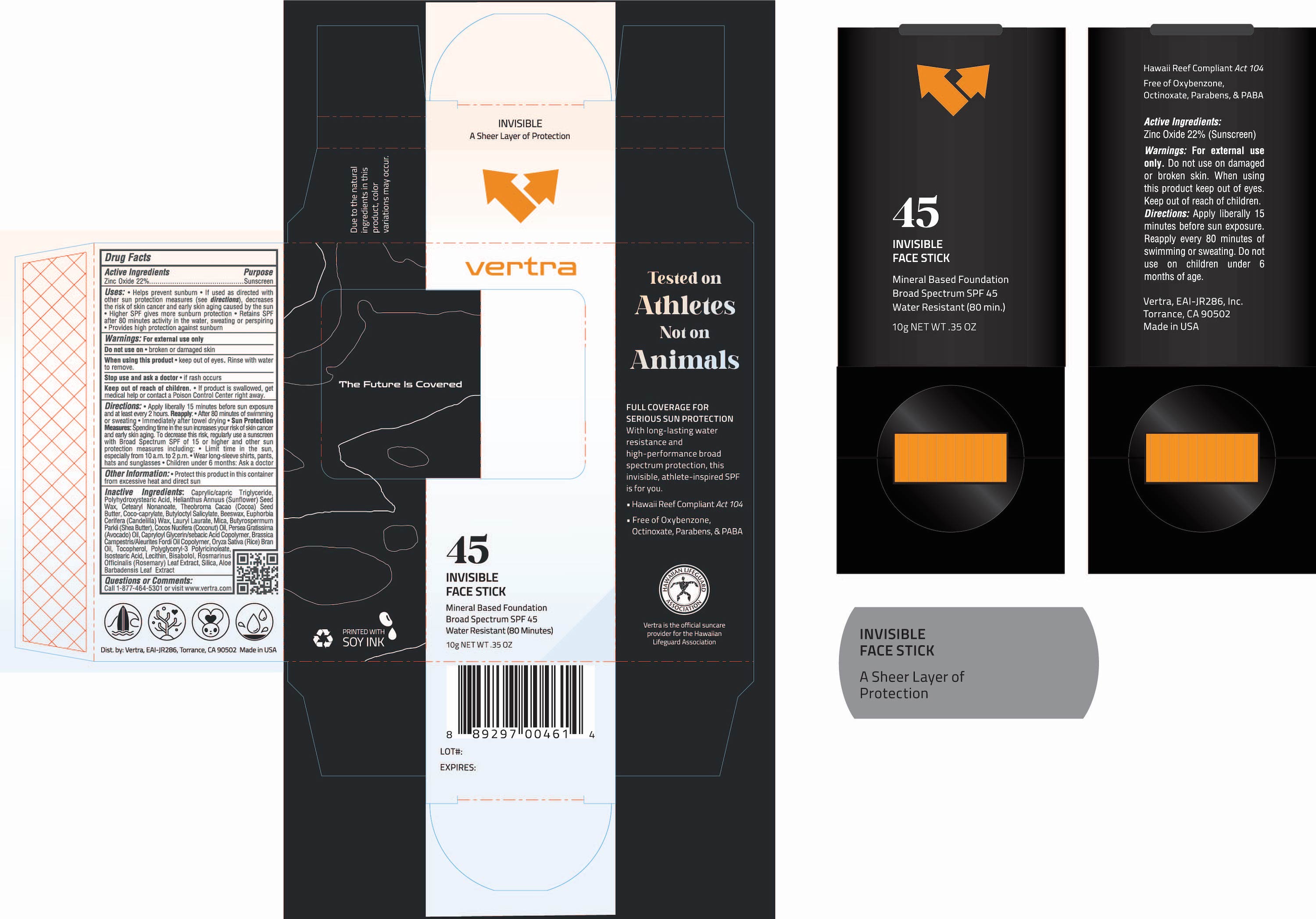 DRUG LABEL: Clear Sunscreen Face Stick Broad Spectrum SPF 45
NDC: 71014-092 | Form: STICK
Manufacturer: Eai-jr 286, Inc
Category: otc | Type: HUMAN OTC DRUG LABEL
Date: 20241022

ACTIVE INGREDIENTS: ZINC OXIDE 22 g/100 g
INACTIVE INGREDIENTS: TOCOPHEROL; LEVOMENOL; HELIANTHUS ANNUUS SEED WAX; BUTYLOCTYL SALICYLATE; POLYHYDROXYSTEARIC ACID (2300 MW); CETEARYL NONANOATE; CANDELILLA WAX; YELLOW WAX; LAURYL LAURATE; MICA; AVOCADO OIL; ALOE VERA LEAF; COCOA BUTTER; SILICON DIOXIDE; MEDIUM-CHAIN TRIGLYCERIDES; POLYGLYCERYL-3 PENTARICINOLEATE; ISOSTEARIC ACID; LECITHIN, SOYBEAN; ROSEMARY; RICE BRAN OIL; COCO-CAPRYLATE; SHEA BUTTER; COCONUT OIL; CAPRYLOYL GLYCERIN/SEBACIC ACID COPOLYMER (2000 MPA.S)

Clear Sunscreen Face Stick Broad Spectrum SPF 45

Active Ingredients Purpose

Zinc Oxide 22% Sunscreen

PURPOSE

- Helps prevent sunburn
- If used as directed with other sun protection measures (see Directions), decreases the risk of skin cancer and early skin aging caused by the sun
- Higher SPF gives more sunburn protection
- Retains SPF after 80 minutes activity in the water, sweating, or perspiring.
- Provides high protection against sunburn

Keep out of reach of children:

- If product is swallowed, get medical help or contact a Poison Control Center right away.

Stop use and ask a doctor if:

- Rash or irritation develops and lasts

Warnings

Do not use:

- On damaged or broken skin

When using this product:

- keep out of eyes. Rinse with water tp remove

For external use only

Directions

- Apply liberally and generously 15 minutes before sun exposure and at least every 2 hours.
- Children under 6 months of age: ask a doctor
- Sun Protection Measures

Spending time in the sun increases your risk of skin cancer and early skin aging. To decrease this risk, regularly use a sunscreen with a broad spectrum SPF value of 15 or higher and other sun protection measures including:

- Limit your time in the sun, especially from 10 a.m. - 2 p.m.
- Wear long-sleeved shirts, pants, hats, and sun glasses
- Reapply:
- After 80 minutes of swimming or sweating
- Immediately after towel drying
- At least every 2 hours

Other Information

- Protect this product in this container from excessive heat and direct sun

Inactive Ingredients

Caprylic/Capric Triglyceride, Polyhydroxystearic Acid, Helianthus Annuus (Sunflower) Seed Wax, Cetearyl Nonanoate, Theobroma Cocoa (Cocoa) Seed Butter, Coco-Caprylate, Butyloctyl Salicylate, Beeswax, Euphorbia Cerifera (Candelilla) Wax, Lauryl Laurate, Mica, Butyrospermum Parkii (Shea Butter), Cocos Nucifera (Coconut) Oil, Persea Gratissima (Avocado) Oil, Capryloyl Glycerin/Sebacic Acid Copolymer, Brassica Campestris/Aleurites Fordi Oil Copolymer, Oryza Sativa (Rice) Bran Oil, Tocopherol, Polyglycerl-3 Polyricinoleate, Isostearic Acid, Lecithin, Bisabolol, Rosemarinus Officinalis (Rosemary) Leaf Extract, Silica, Aloe Barbadensis Leaf Extract

PACKAGE LABEL

vertra

45

Invisible Face Stick

Mineral Based Foundation

Broad Spectrum SPF 45

Water Resistant (80 minutes)

10g NET WT. 0.35 OZ.